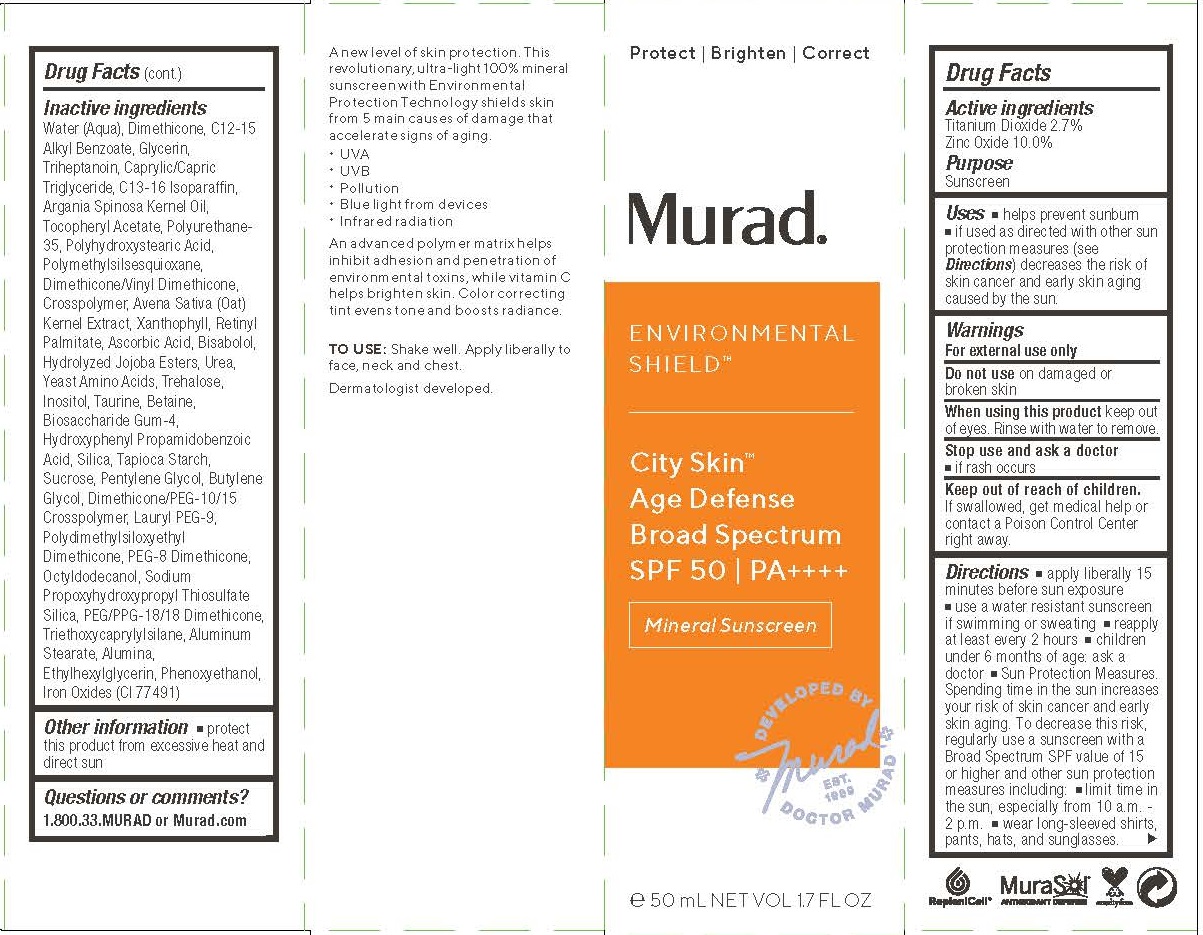 DRUG LABEL: MURAD - ENVIRONMENTAL SHIELD - CITY SKIN AGE DEFENSE BROAD SPECTRUM 
NDC: 70381-102 | Form: LOTION
Manufacturer: Murad, LLC
Category: otc | Type: HUMAN OTC DRUG LABEL
Date: 20200414

ACTIVE INGREDIENTS: TITANIUM DIOXIDE 2.7 g/100 mL; ZINC OXIDE 10 g/100 mL
INACTIVE INGREDIENTS: WATER; DIMETHICONE; ALKYL (C12-15) BENZOATE; GLYCERIN; TRIHEPTANOIN; MEDIUM-CHAIN TRIGLYCERIDES; C13-16 ISOPARAFFIN; ARGAN OIL; .ALPHA.-TOCOPHEROL ACETATE; POLYURETHANE-34 (40 MPA, TENSILE STRENGTH OF FILM AT BREAK); POLYHYDROXYSTEARIC ACID (2300 MW); POLYMETHYLSILSESQUIOXANE (11 MICRONS); DIMETHICONE/VINYL DIMETHICONE CROSSPOLYMER (SOFT PARTICLE); OAT; LUTEIN; VITAMIN A PALMITATE; ASCORBIC ACID; LEVOMENOL; HYDROLYZED JOJOBA ESTERS (ACID FORM); UREA; AMINO ACIDS, SOURCE UNSPECIFIED; TREHALOSE; INOSITOL; TAURINE; BETAINE; BIOSACCHARIDE GUM-4; HYDROXYPHENYL PROPAMIDOBENZOIC ACID; SILICON DIOXIDE; STARCH, TAPIOCA; SUCROSE; PENTYLENE GLYCOL; BUTYLENE GLYCOL; LAURYL PEG-9 POLYDIMETHYLSILOXYETHYL DIMETHICONE; PEG-8 DIMETHICONE; OCTYLDODECANOL; SODIUM PROPOXYHYDROXYPROPYL THIOSULFATE SILICA; PEG/PPG-18/18 DIMETHICONE; TRIETHOXYCAPRYLYLSILANE; ALUMINUM STEARATE; ALUMINUM OXIDE; ETHYLHEXYLGLYCERIN; PHENOXYETHANOL

MURAD - ENVIRONMENTAL SHIELD - CITY SKIN AGE DEFENSE BROAD SPECTRUM SPF 50

ACTIVE INGREDIENTS

Titanium Dioxide 2.7%
Zinc Oxide 10.0%

PURPOSE

SUNSCREEN

USES

- helps prevent sunburn
- if used as directed with other sun protection measures (see Directions) decreases the risk ofskin cancer and early skin agingcaused by the sun.

WARNINGS

For external use only
Do not use on damaged or broken skin
When using this product keep out of eyes. Rinse with water to remove.
Stop use and ask a doctor

- if rash occurs

Keep out of reach of children. If product is swallowed, get medical help or contact a Poison Control Center right away.

DIRECTIONS

- apply liberally 15 minutes before sun exposure
- use a water resistant sunscreen if swimming or sweating
- reapply at least every 2 hours
- children under 6 months of age: ask a doctor
- Sun Protection Measures.pending time in the sun increases your risk of skin cancer and early skin aging. To decrease this risk, regularly use a sunscreen with a Broad Spectrum SPF value of 15 or higher and other sun protection measures including:
- limit time in the sun, especially from 10 a.m. - 2 p.m.
- wear long-sleeved shirts, pants, hats, and sunglasses.

INACTIVE INGREDIENTS

Water (Aqua), Dimethicone, C12-15 Alkyl Benzoate, Glycerin, Triglyceride, C13-16 Isoparaffin, Argania Spinosa Kernel Oil,
Tocopheryl Acetate, Polyurethane-35, Polyhydroxystearic Acid, Polymethylsilsesquioxane, Dimethicone/Vinyl Dimethicone,
Crosspolymer, Avena Sativa (Oat) Kernel Extract, Xanthophyll, Retinyl Palmitate, Ascorbic Acid, Bisabolol, Hydrolyzed Jojoba Esters, Urea, Yeast Amino Acids, Trehalose, Inositol, Taurine, Betaine, Biosaccharide Gum-4, Hydroxyphenyl Propamidobenzoic
Acid, Silica, Tapioca Starch, Sucrose, Pentylene Glycol, Butylene Glycol, Dimethicone/PEG-10/15 Crosspolymer, Lauryl PEG-9,
Polydimethylsiloxyethyl Dimethicone, PEG-8 Dimethicone, Octyldodecanol, Sodium Propoxyhydroxypropyl Thiosulfate Silica, PEG/PPG-18/18 Dimethicone, Triethoxycaprylylsilane, Aluminum Stearate, Alumina, Ethylhexylglycerin, Phenoxyethanol, Iron Oxides (CI 77491)

OTHER INFORMATION

- protect this product from excessive heat and direct sun

QUESTIONS OR COMMENTS?

1.800.33.MURAD or Murad.com